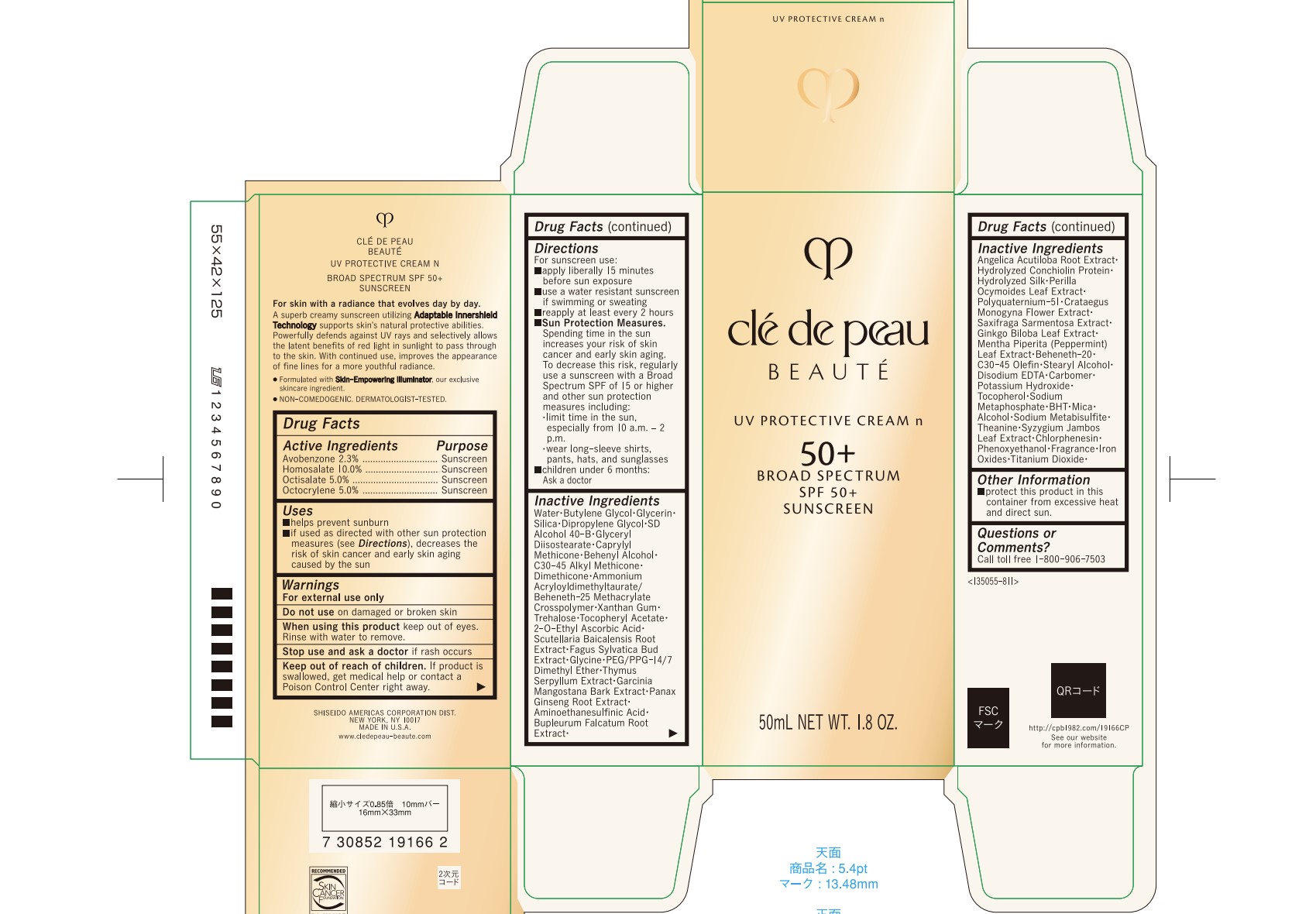 DRUG LABEL: cle de peau BEAUTE UV PROTECTIVE N
NDC: 58411-905 | Form: CREAM
Manufacturer: Shiseido Americas Corporation
Category: otc | Type: HUMAN OTC DRUG LABEL
Date: 20250507

ACTIVE INGREDIENTS: AVOBENZONE 1201 mg/50 mL; HOMOSALATE 5225 mg/50 mL; OCTISALATE 2612 mg/50 mL; OCTOCRYLENE 2612 mg/50 mL
INACTIVE INGREDIENTS: WATER; BUTYLENE GLYCOL; GLYCERIN; SILICA; DIPROPYLENE GLYCOL; GLYCERYL DIISOSTEARATE; CAPRYLYL METHICONE; BEHENYL ALCOHOL; C30-45 ALKYL METHICONE; DIMETHICONE; AMMONIUM ACRYLOYLDIMETHYLTAURATE/BEHENETH-25 METHACRYLATE CROSSPOLYMER (52000 MPA.S); XANTHAN GUM; TREHALOSE; .ALPHA.-TOCOPHEROL ACETATE, DL-; 2-O-ETHYL ASCORBIC ACID; SCUTELLARIA BAICALENSIS ROOT; FAGUS SYLVATICA FLOWER BUD; GLYCINE; PEG/PPG-14/7 DIMETHYL ETHER; THYMUS SERPYLLUM WHOLE; GARCINIA MANGOSTANA BARK; ASIAN GINSENG; AMINOMETHANESULFONIC ACID; BUPLEURUM FALCATUM ROOT; ANGELICA ACUTILOBA ROOT; PERILLA FRUTESCENS LEAF; POLYQUATERNIUM-51 (2-METHACRYLOYLOXYETHYL PHOSPHORYLCHOLINE/N-BUTYL METHACRYLATE; 3:7); CRATAEGUS MONOGYNA FLOWER; SAXIFRAGA STOLONIFERA LEAF; GINKGO; MENTHA PIPERITA LEAF; BEHENETH-20; C30-45 OLEFIN; STEARYL ALCOHOL; EDETATE DISODIUM; CARBOMER HOMOPOLYMER, UNSPECIFIED TYPE; POTASSIUM HYDROXIDE; TOCOPHEROL; SODIUM METAPHOSPHATE; BUTYLATED HYDROXYTOLUENE; MICA; ALCOHOL; SODIUM METABISULFITE; THEANINE; SYZYGIUM JAMBOS LEAF; CHLORPHENESIN; PHENOXYETHANOL; FERRIC OXIDE RED; FERRIC OXIDE YELLOW; TITANIUM DIOXIDE; FERROSOFERRIC OXIDE

cle de peau BEAUTE UV PROTECTIVE CREAM N

Drug Facts

ACTIVE INGREDIENT

Active Ingredients | Purpose
Avobenzone 2.3% | Sunscreen
Homosalate 10.0% | Sunscreen
Octisalate 5.0% | Sunscreen
Octocrylene 5.0% | Sunscreen

Uses

- helps prevent sunburn
- if used as directed with other sun protection measures (see Directions), decreases the risk of skin cancer and early skin aging caused by the sun

Warnings

For external use only

Do not useon damaged or broken skin

WHEN USING

When using this productkeep out of eyes. Rinse with water to remove.

Stop use and ask a doctorif rash occurs.

Keep out of reach of children.If product is swallowed, get medical help or contact a Poison Control Center right away.

Directions

For sunscreen use:

- apply liberally 15 minutes before sun exposure
- use a water resistant sunscreen if swimming or sweating
- reapply at least every 2 hours
- Sun Protection Measures.Spending time in the sun increases your risk of skin cancer and early skin aging. To decrease this risk, regularly use a sunscreen with a Broad Spectrum SPF of 15 or higher and other sun protection measures including:
- limit time in the sun, especially from 10 a.m. – 2 p.m.
- wear long-sleeve shirts, pants, hats, and sunglasses
- children under 6 months: Ask a doctor

Inactive Ingredients

WATER･BUTYLENE GLYCOL･GLYCERIN･SILICA･DIPROPYLENE GLYCOL･SD ALCOHOL 40-B･GLYCERYL DIISOSTEARATE･CAPRYLYL METHICONE･BEHENYL ALCOHOL･C30-45 ALKYL METHICONE･DIMETHICONE･AMMONIUM ACRYLOYLDIMETHYLTAURATE/BEHENETH-25 METHACRYLATE CROSSPOLYMER･XANTHAN GUM･TREHALOSE･TOCOPHERYL ACETATE･2-O-ETHYL ASCORBIC ACID･SCUTELLARIA BAICALENSIS ROOT EXTRACT･FAGUS SYLVATICA BUD EXTRACT･GLYCINE･PEG/PPG-14/7 DIMETHYL ETHER･THYMUS SERPYLLUM EXTRACT･GARCINIA MANGOSTANA BARK EXTRACT･PANAX GINSENG ROOT EXTRACT･AMINOETHANESULFINIC ACID･BUPLEURUM FALCATUM ROOT EXTRACT･ANGELICA ACUTILOBA ROOT EXTRACT･HYDROLYZED CONCHIOLIN PROTEIN･HYDROLYZED SILK･PERILLA OCYMOIDES LEAF EXTRACT･POLYQUATERNIUM-51･CRATAEGUS MONOGYNA FLOWER EXTRACT･SAXIFRAGA SARMENTOSA EXTRACT･GINKGO BILOBA LEAF EXTRACT･MENTHA PIPERITA (PEPPERMINT) LEAF EXTRACT･BEHENETH-20･C30-45 OLEFIN･STEARYL ALCOHOL･DISODIUM EDTA･CARBOMER･POTASSIUM HYDROXIDE･TOCOPHEROL･SODIUM METAPHOSPHATE･BHT･MICA･ALCOHOL･SODIUM METABISULFITE･THEANINE･SYZYGIUM JAMBOS LEAF EXTRACT･CHLORPHENESIN･PHENOXYETHANOL･FRAGRANCE･IRON OXIDES･TITANIUM DIOXIDE･

Other information

- protect this product in this container from excessive heat and direct sun.

Questions or comments?

Call toll free 1-800-906-7503